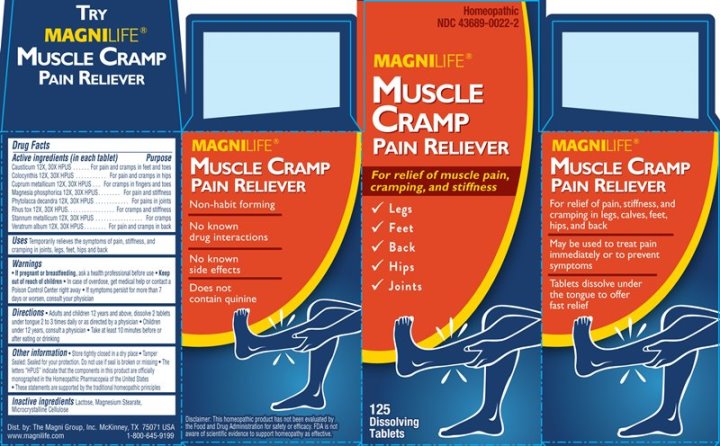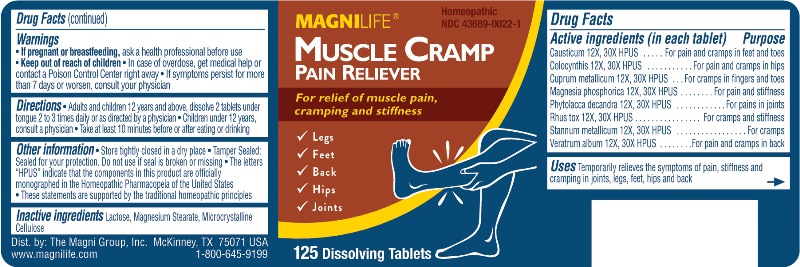 DRUG LABEL: Muscle Cramp Pain Reliever
NDC: 43689-0022 | Form: TABLET
Manufacturer: The Magni Company
Category: homeopathic | Type: HUMAN OTC DRUG LABEL
Date: 20241105

ACTIVE INGREDIENTS: CAUSTICUM 12 [hp_X]/1 1; CITRULLUS COLOCYNTHIS FRUIT PULP 12 [hp_X]/1 1; COPPER 12 [hp_X]/1 1; MAGNESIUM PHOSPHATE, DIBASIC TRIHYDRATE 12 [hp_X]/1 1; PHYTOLACCA AMERICANA ROOT 12 [hp_X]/1 1; TOXICODENDRON PUBESCENS LEAF 12 [hp_X]/1 1; TIN 12 [hp_X]/1 1; VERATRUM ALBUM ROOT 12 [hp_X]/1 1
INACTIVE INGREDIENTS: LACTOSE MONOHYDRATE; MAGNESIUM STEARATE; MICROCRYSTALLINE CELLULOSE

DRUG FACTS:

ACTIVE INGREDIENTS

Causticum, Colocynthis, Cuprum Metallicum, Magnesia Phosphorica, Phytolacca Decandra, Rhus Tox, Stannum Metallicum, Veratrum Album

INDICATIONS

Temporarily relieves the symptoms of pain, stiffness and cramping in joints, legs, feet, hips and back.

WARNINGS

If pregnant or breastfeeding, ask a health professional before use.

Keep out of reach of children. In case of overdose, get medical help or contact a Poison Control Center right away. Is symptoms persist for more than 7 days or worsens, consult your physician.

KEEP OUT OF REACH OF CHILDREN

In case of overdose, get medical help or contact a Poison Control Center right away. If symptoms persist for more than 7 days or worsens, consult your physician.

DIRECTIONS

Adults and children 12 years and above, dissolve 2 tablets under tongue 2 to 3 times daily or as directed by a physician.

Children under 12 years of age, consult a physician. Take at least 10 minutes before or after eating or drinking.

INDICATIONS AND USAGE

Temporarily relieves the symptoms of pain, stiffness and cramping in joints, legs, hips and back.

INACTIVE INGREDIENTS

Lactose, Magnesium Stearate, Microcrystalline Cellulose.

QUESTIONS

Dist. by:

The Magni Group, Inc. McKinney, TX 75071 USA

www.magnilife.com 1-800-645-9199

PACKAGE LABEL:

MAGNILIFE

Homeopathic

NDC 43689-0022-1

MUSCLE CRAMP PAIN RELIEVER

For relief of muscle pain, cramping and stiffness,

√Legs

√Feet

√Back

√Hips

√Joints

125 Dissolving Tablets